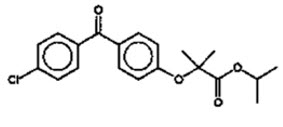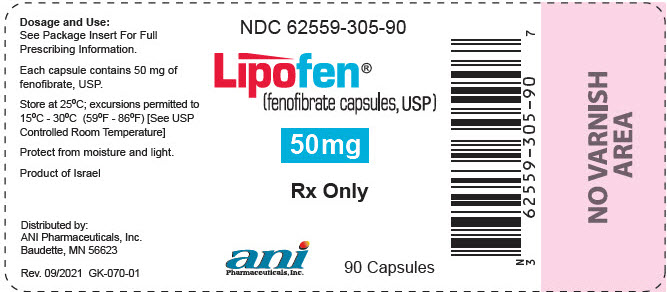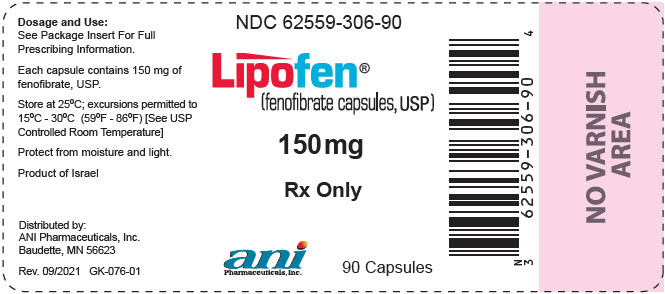 DRUG LABEL: Lipofen
NDC: 62559-305 | Form: CAPSULE
Manufacturer: ANI Pharmaceuticals, Inc.
Category: prescription | Type: HUMAN PRESCRIPTION DRUG LABEL
Date: 20250618

ACTIVE INGREDIENTS: FENOFIBRATE 50 mg/1 1
INACTIVE INGREDIENTS: LAUROYL PEG-32 GLYCERIDES; POLYETHYLENE GLYCOL 20000; POLYETHYLENE GLYCOL 8000; HYDROXYPROPYL CELLULOSE (160000 WAMW); SODIUM STARCH GLYCOLATE TYPE A; GELATIN, UNSPECIFIED; TITANIUM DIOXIDE; SHELLAC; PROPYLENE GLYCOL; FERROSOFERRIC OXIDE; FD&C BLUE NO. 1; FD&C BLUE NO. 2; FD&C RED NO. 40; D&C YELLOW NO. 10

HIGHLIGHTS OF PRESCRIBING INFORMATION

These highlights do not include all the information needed to use LIPOFEN® safely and effectively. See full prescribing information for LIPOFEN®.
LIPOFEN® (fenofibrate) capsules, for oral use
Initial U.S. Approval: 1993

RECENT MAJOR CHANGES

Indications and Usage (1) | 6/2025
Dosage and Administration (2) | 6/2025
Warnings and Precautions, Mortality and Coronary Heart Disease Morbidity (5.1) | 6/2025

1 INDICATIONS AND USAGE

LIPOFEN is a peroxisome proliferator-activated receptor (PPAR) alpha agonist indicated as an adjunct to diet:

- to reduce triglyceride (TG) levels in adults with severe hypertriglyceridemia (TG greater than or equal to 500 mg/dL) (1).
- to reduce elevated low-density lipoprotein cholesterol (LDL-C) in adults with primary hyperlipidemia when use of recommended LDL-C lowering therapy is not possible (1)

Limitations of Use:

- Markedly elevated levels of serum TG (e.g., >2,000 mg/dL) may increase the risk of developing pancreatitis. The effect of fenofibrate therapy on reducing this risk has not been determined (1).
- Fenofibrate did not reduce coronary heart disease morbidity and mortality in two large, randomized controlled trials of patients with type 2 diabetes mellitus. (1)

2 DOSAGE AND ADMINISTRATION

- Severe hypertriglyceridemia: 50 to 150 mg orally once daily; the dosage should be adjusted according to patient response (2.2)
- Primary hyperlipidemia: 150 mg orally once daily (2.2)
- Administer as a single dose, at any time of day, with food 2.2).
- Assess TG when clinically appropriate, as early as 4 to 8 weeks after initiating LIPOFEN. Discontinue LIPOFEN in patients who do not have an adequate response after 2 months of treatment (2.2)
- Renal impairment: Initial dosage of 50 mg orally once daily (2.3)
- Geriatric patients: Select the dosage on the basis of renal function (2.4)

3 DOSAGE FORMS AND STRENGTHS

Capsules: 50 mg and 150 mg (3)

4 CONTRAINDICATIONS

- Severe renal impairment, including those with end-stage renal disease (ESRD) and those receiving dialysis (4)
- Active liver disease, including those with unexplained persistent liver function abnormalities (4)
- Pre-existing gallbladder disease (4)
- Hypersensitivity to fenofibrate, fenofibric acid, or any of the excipients in LIPOFEN (4)

5 WARNINGS AND PRECAUTIONS

- Hepatotoxicity: Serious drug-induced liver injury, including liver transplantation and death, has been reported with fenofibrates, including LIPOFEN. Monitor patient's liver function, including serum ALT, AST, and total bilirubin, at baseline and periodically for the duration of therapy. Discontinue if signs or symptoms of liver injury develop or if elevated enzyme levels persist. (5.2)
- Myopathy and Rhabdomyolysis: Have been reported in patients taking fenofibrates. Risks are increased during co-administration with a statin, in geriatric patients and in patients with renal impairment, or hypothyroidism. Discontinue LIPOFEN if markedly elevated CK levels occur or if myopathy is either diagnosed or suspected. Temporarily discontinue LIPOFEN in patients experiencing an acute or serious condition at high risk of developing renal failure secondary to rhabdomyolysis. Inform patients of the risk of myopathy and rhabdomyolysis when starting or increasing the LIPOFEN dosage. Instruct patients to promptly report any unexplained muscle pain, tenderness, or weakness, particularly if accompanied by malaise or fever. (5.3)
- Increases in Serum Creatinine: Monitor renal function in patients with renal impairment taking LIPOFEN. Consider monitoring renal function in patients at risk for renal impairment. (5.4)
- Cholelithiasis: Fenofibrate may increase cholesterol excretion into the bile, leading to cholelithiasis. If cholelithiasis is suspected, gallbladder studies are indicated. (5.5)
- Hypersensitivity Reactions: Acute hypersensitivity reactions, including anaphylaxis and angioedema and delayed hypersensitivity reactions, including severe cutaneous adverse drug reactions have been reported postmarketing. Some cases were life-threatening and required emergency treatment. Discontinue LIPOFEN and treat appropriately if reactions occur. (5.9)

6 ADVERSE REACTIONS

Adverse reactions (≥ 2% and greater than placebo): abnormal liver tests, increased AST, increased ALT, increased CPK, and rhinitis (6.1).

To report SUSPECTED ADVERSE REACTIONS, contact ANI Pharmaceuticals, Inc. at 1-800-308-6755 or FDA at 1-800-FDA-1088 or www.fda.gov/medwatch.

7 DRUG INTERACTIONS

- Consider if the benefit of concomitant use of statins or colchicine outweighs the increased risk of myopathy and rhabdomyolysis. Monitor patients for signs and symptoms of myopathy (7)
- Exercise caution in concomitant treatment with coumarin anticoagulants. Reduce the dosage of coumarin to maintain the PT/INR at the desired level to prevent bleeding complications (7).
- Consider the benefits and risks of concomitant use with immunosuppressants and other potentially nephrotoxic agents. Use the lowest effective dosage and monitor renal function (7).
  Administer LIPOFEN at least 1 hour before or 4 to 6 hours after a bile acid resin to avoid impeding its absorption (7).

FULL PRESCRIBING INFORMATION

1 INDICATIONS AND USAGE

LIPOFEN is indicated as adjunctive therapy to diet:

- to reduce triglyceride (TG) levels in adults with severe hypertriglyceridemia (TG greater than or equal to 500 mg/dL).
- to reduce elevated low-density lipoprotein cholesterol (LDL-C) in adults with primary hyperlipidemia when use of recommended LDL-C lowering therapy is not possible.

Limitations of Use

- Markedly elevated levels of serum TG (e.g., ≥ 2,000 mg/dL) may increase the risk of developing pancreatitis. The effect of fenofibrate therapy on reducing this risk has not been determined [see Warnings and Precautions (5.7)].
- Fenofibrate did not reduce coronary heart disease morbidity and mortality in two large, randomized controlled trials of patients with type 2 diabetes mellitus [see Warnings and Precautions (5.1) and Clinical Studies (14.4)].

2 DOSAGE AND ADMINISTRATION

2.1 Prior to Initiation of LIPOFEN

- Assess lipid levels before initiating therapy. Identify other causes (e.g., diabetes mellitus, hypothyroidism, or medications) of high TG levels and manage as appropriate.
- Patients should be placed on an appropriate lipid-lowering diet before receiving LIPOFEN, and should continue this diet during treatment with LIPOFEN.
- In patients with diabetes and fasting chylomicronemia, improve glycemic control prior to considering starting LIPOFEN.

2.2 Recommended Dosage and Administration

- Severe hypertriglyceridemia:
  - The recommended dosage of LIPOFEN is 50 mg or 150 mg orally once daily.
  - Dosage should be individualized according to patient response, and should be adjusted if necessary following repeat lipid determinations at 4 to 8 week intervals.
- Primary hyperlipidemia:
  - The recommended dosage of LIPOFEN is 150 mg orally once daily.
- Administer LIPOFEN as a single dose at any time of day, with food.
- Advise patients to swallow LIPOFEN capsules whole. Do not crush, break, dissolve, or chew capsules.
- Assess TG when clinically appropriate, as early as 4 to 8 weeks after initiating LIPOFEN. Discontinue LIPOFEN in patients who do not have an adequate response after 2 months of treatment.
- If a dose is missed, advise patients not to take an extra dose. Resume treatment with the next dose.
- Advise patients to take LIPOFEN at least 1 hour before or 4 hours to 6 hours after a bile acid binding resin to avoid impeding its absorption.

2.3 Recommended Dosage in Patients with Renal Impairment

- Assess renal function prior to initiation of LIPOFEN and periodically thereafter [see Warnings and Precautions (5.4)].
- Treatment with LIPOFEN should be initiated at a dosage of 50 mg orally once daily in patients with mild to moderately impaired renal function (eGFR 30 to <60 mL/min/1.73m^2), and increased only after evaluation of the effects on renal function and TG levels at this dosage.
- LIPOFEN is contraindicated in patients with severe renal impairment (eGFR <30 mL/min/1.73m^2), including those with end-stage renal disease (ESRD) and those receiving dialysis [see Use in Specific Populations (8.6) and Clinical Pharmacology (12.3)].

2.4 Recommended Dosage in Geriatric Patients

Dosage selection for geriatric patients should be made on the basis of renal function [see Use in Specific Populations (8.5) and Clinical Pharmacology (12.3)].

3 DOSAGE FORMS AND STRENGTHS

- 50 mg: Size 3 white opaque gelatin capsule imprinted "G 246" and "50" in black ink.
- 150 mg: Size 1 white opaque gelatin capsule imprinted "G 248" and "150" in green ink.

4 CONTRAINDICATIONS

LIPOFEN is contraindicated in patients with:

- Severe renal impairment, including those with end-stage renal disease (ESRD) and those receiving dialysis [see Clinical Pharmacology (12.3)].
- Active liver disease, including those with unexplained persistent liver function abnormalities [see Warnings and Precautions (5.2)].
- Pre-existing gallbladder disease [see Warnings and Precautions (5.5)].
- Hypersensitivity to fenofibrate, fenofibric acid, or any of the excipients in LIPOFEN. Serious hypersensitivity reactions including anaphylaxis and angioedema have been reported with fenofibrate [see Warnings and Precautions (5.9)].

5 WARNINGS AND PRECAUTIONS

5.1 Mortality and Coronary Heart Disease Morbidity

Fenofibrate did not reduce cardiovascular disease morbidity or mortality in two large, randomized controlled trials of patients with type 2 diabetes mellitus [see Clinical Studies (14.4)].

Because of chemical, pharmacological, and clinical similarities between fenofibrates, including LIPOFEN; pemafibrate; clofibrate; and gemfibrozil; the findings in 5 large randomized, placebo-controlled clinical trials with these other fibrate drugs may also apply to LIPOFEN.

Pemafibrate did not reduce cardiovascular disease morbidity or mortality in a large, randomized, placebo-controlled trial of patients with type 2 diabetes mellitus on background statin therapy [see Clinical Studies (14.4)].

In the Coronary Drug Project, a large trial conducted from 1965 to 1985 in men post myocardial infarction, there was no difference in mortality or nonfatal myocardial infarction between the clofibrate group and the placebo group after 5 years of treatment (NCT00000482).

In a trial conducted by the World Health Organization (WHO) from 1965 to 1976, men without known coronary artery disease were treated with placebo or clofibrate for 5 years and followed for an additional 1 year. There was a statistically significant, higher age-adjusted all-cause mortality in the clofibrate group compared with the placebo group (5.70% vs. 3.96%, p≤0.01). Excess mortality was due to a 33% increase in non-cardiovascular causes, including malignancy, post-cholecystectomy complications, and pancreatitis.

The Helsinki Heart Study, conducted from 1982 to 1987, was a large (n=4,081) trial of middle-aged men without a history of coronary artery disease. Subjects received either placebo or gemfibrozil for 5 years, with a 3.5-year open extension afterward. Total mortality was numerically but not statistically higher in the gemfibrozil randomization group versus placebo [95% confidence interval (CI) of the hazard ratio (HR) 0.91 to 1.64].

A secondary prevention component of the Helsinki Heart Study treated middle-aged men with gemfibrozil or placebo for 5 years. The HR for cardiac deaths was 2.2, 95% CI, 0.94 to 5.05.

5.2 Hepatotoxicity

Serious drug-induced liver injury (DILI), including liver transplantation and death, has been reported with postmarketing use of fenofibrates, including LIPOFEN. DILI has been reported within the first few weeks of treatment or after several months of therapy and in some cases has reversed with discontinuation of LIPOFEN treatment. Patients with DILI have experienced signs and symptoms including dark urine, abnormal stool, jaundice, malaise, abdominal pain, myalgia, weight loss, pruritus, and nausea. Many patients had concurrent elevations of total bilirubin, serum alanine transaminase (ALT), and aspartate transaminase (AST). DILI has been characterized as hepatocellular, chronic active, and cholestatic hepatitis, and cirrhosis has occurred in association with chronic active hepatitis.

In clinical trials, an intermediate daily dosage or the maximum recommended daily dosage of fenofibrate have been associated with increases in serum AST or ALT. The incidence of increases in transaminases may be dose related [see Adverse Reactions (6.1)].

LIPOFEN is contraindicated in patients with active liver disease, including those with unexplained persistent liver function abnormalities. Monitor patient's liver function, including serum ALT, AST, and total bilirubin, at baseline and periodically for the duration of therapy with LIPOFEN. Discontinue LIPOFEN if signs or symptoms of liver injury develop or if elevated enzyme levels persist (ALT or AST > 3 times the upper limit of normal, or if accompanied by elevation of bilirubin). Do not restart LIPOFEN in these patients if there is no alternative explanation for the liver injury.

5.3 Myopathy and Rhabdomyolysis

LIPOFEN may cause myopathy [muscle pain, tenderness, or weakness associated with elevated creatine kinase (CK)] and rhabdomyolysis.

Risk Factors for Myopathy

Risk factors for myopathy include age 65 years or older, uncontrolled hypothyroidism, renal impairment, and concomitant use with certain other drugs [see Drug Interactions (7) and Use in Specific Populations (8.6)].

Steps to Prevent or Reduce the Risk of Myopathy and Rhabdomyolysis

Data from observational studies indicate that the risk for rhabdomyolysis is increased when fibrates, including fenofibrates, are co-administered with a statin. Avoid concomitant use unless the benefit of further alterations in TG levels is likely to outweigh the increased risk of this drug combination [see Drug Interactions (7), Clinical Pharmacology (12.3), and Clinical Studies (14.4)].

Cases of myopathy, including rhabdomyolysis, have been reported with fenofibrates, including LIPOFEN, co-administered with colchicine. Consider whether the benefit of using colchicine concomitantly with LIPOFEN outweighs the increased risk of myopathy [see Drug Interactions (7)].

Discontinue LIPOFEN if markedly elevated CK levels occur or if myopathy is either diagnosed or suspected. Muscle symptoms and CK elevations may resolve if LIPOFEN is discontinued. Temporarily discontinue LIPOFEN in patients experiencing an acute or serious condition at high risk of developing renal failure secondary to rhabdomyolysis (e.g., sepsis; shock; severe hypovolemia; major surgery; trauma; severe metabolic, endocrine, or electrolyte disorders; or uncontrolled epilepsy).

Inform patients of the risk of myopathy and rhabdomyolysis when starting or increasing the LIPOFEN dosage. Instruct patients to promptly report any unexplained muscle pain, tenderness or weakness, particularly if accompanied by malaise or fever.

5.4 Increases in Serum Creatinine

Increases in serum creatinine have been reported in patients receiving fenofibrates. These increases tend to return to baseline following discontinuation of LIPOFEN. The clinical significance of this finding is unknown. Monitor renal function in patients with renal impairment taking LIPOFEN. Renal monitoring should also be considered for patients taking LIPOFEN at risk for renal insufficiency, such as geriatric patients and patients with diabetes. LIPOFEN is contraindicated in patients with severe renal impairment, including those with end-stage renal disease (ESRD) and those receiving dialysis [see Dosage and Administration (2.3), Use in Specific Populations (8.6), and Clinical Pharmacology (12.3)].

5.5 Cholelithiasis

Fenofibrate may increase cholesterol excretion into the bile, leading to cholelithiasis. If cholelithiasis is suspected, gallbladder studies are indicated. LIPOFEN therapy should be discontinued if gallstones are found. LIPOFEN is contraindicated in patients with pre-existing gallbladder disease.

5.6 Increased Bleeding Risk with Coumarin Anticoagulants

Exercise caution when co-administering anticoagulants with LIPOFEN because of the potentiation of coumarin-type anticoagulant effects in prolonging the prothrombin time/International Normalized Ratio (PT/INR). To prevent bleeding complications, monitor the PT/INR frequently and adjust the dosage of the anticoagulant until the PT/INR has stabilized [see Drug Interactions (7)].

5.7 Pancreatitis

Pancreatitis has been reported in patients taking fenofibrates. This occurrence may represent a failure of efficacy in patients with severe hypertriglyceridemia, a direct drug effect, or a secondary phenomenon mediated through biliary tract stone or sludge formation with obstruction of the common bile duct.

5.8 Hematologic Changes

Mild to moderate hemoglobin, hematocrit, and white blood cell decreases have been observed in patients following initiation of therapy with fenofibrates. However, these levels stabilize during long-term administration. Thrombocytopenia and agranulocytosis have been reported in individuals treated with LIPOFEN. Periodic monitoring of red and white blood cell counts is recommended during the first 12 months of LIPOFEN administration.

5.9 Hypersensitivity Reactions

Acute Hypersensitivity

Anaphylaxis and angioedema have been reported with postmarketing use of fenofibrates. In some cases, reactions were life-threatening and required emergency treatment. If a patient develops signs or symptoms of an acute hypersensitivity reaction, advise them to seek immediate medical attention and discontinue LIPOFEN. LIPOFEN is contraindicated in patients with a hypersensitivity to fenofibrate, fenofibric acid, or any of the ingredients in LIPOFEN.

Delayed Hypersensitivity

Severe cutaneous adverse drug reactions (SCAR), including Stevens-Johnson syndrome, Toxic Epidermal Necrolysis, and Drug Reaction with Eosinophilia and Systemic Symptoms (DRESS), have been reported with post-marketing use of fenofibrates, occurring days to weeks after treatment initiation. The cases of DRESS were associated with cutaneous reactions (such as rash or exfoliative dermatitis) and a combination of eosinophilia, fever, systemic organ involvement (renal, hepatic, or respiratory). Discontinue LIPOFEN and treat patients appropriately if SCAR is suspected.

5.10 Venothromboembolic Disease

In the Fenofibrate Intervention and Event Lowering in Diabetes (FIELD) trial, pulmonary embolus (PE) and deep vein thrombosis (DVT) were observed at higher rates in the fenofibrate than the placebo-treated group. Of 9,795 patients enrolled in FIELD, there were 4,900 in the placebo group and 4,895 in the fenofibrate group. For DVT, there were 48 events (1%) in the placebo group and 67 (1.4%) in the fenofibrate group (p = 0.074); and for PE, there were 32 (0.7%) events in the placebo group and 53 (1.1%) in the fenofibrate group (p = 0.022).

In the Coronary Drug Project, a higher proportion of the clofibrate group experienced definite or suspected fatal or nonfatal pulmonary embolism or thrombophlebitis than the placebo group (5.2% vs. 3.3% at five years; p<0.01).

In the cardiovascular outcome trial with pemafibrate, pulmonary embolism was reported for 37 (0.7%) subjects in the pemafibrate group and 16 (0.3%) subjects in the placebo group. Deep vein thrombosis was reported for 36 (0.7%) subjects in the pemafibrate group and 13 (0.2%) subjects in the placebo group.

5.11 Paradoxical Decreases in HDL Cholesterol Levels

There have been postmarketing and clinical trial reports of severe decreases in high-density lipoprotein cholesterol (HDL-C) levels (as low as 2 mg/dL) occurring in patients with and without diabetes initiated on fibrate therapy, including fenofibrate. The decrease in HDL-C is mirrored by a decrease in apolipoprotein A1. This decrease has been reported to occur within 2 weeks to years after initiation of fibrate therapy. The HDL-C levels remain depressed until fibrate therapy has been withdrawn; the response to withdrawal of fibrate therapy is rapid and sustained. The clinical significance of this decrease in HDL-C is unknown. Check HDL-C levels within the first few months after initiation of LIPOFEN. If a severely depressed HDL-C level is detected, discontinue LIPOFEN and monitor HDL-C until it has returned to baseline. LIPOFEN should not be re-initiated.

6 ADVERSE REACTIONS

The following serious adverse reactions are described below and elsewhere in the labeling:

- Mortality and coronary heart disease morbidity [see Warnings and Precautions (5.1)]
- Hepatoxicity [see Warnings and Precautions (5.2)]
- Myopathy and Rhabdomyolysis [see Warnings and Precautions (5.3)]
- Increases in Serum Creatinine [see Warnings and Precautions (5.4)]
- Cholelithiasis [see Warnings and Precautions (5.5)]
- Increased Bleeding Risk with Coumarin Anticoagulants [see Warnings and Precautions (5.6)]
- Pancreatitis [see Warnings and Precautions (5.7)]
- Hematologic Changes [see Warnings and Precautions (5.8)]
- Hypersensitivity reactions [see Warnings and Precautions (5.9)]
- Venothromboembolic disease [see Warnings and Precautions (5.10)]
- Paradoxical Decreases in HDL Cholesterol Levels [see Warnings and Precautions (5.11)]

6.1 Clinical Trials Experience

Because clinical trials are conducted under widely varying conditions, adverse reaction rates observed in the clinical trials of a drug cannot be directly compared to rates in the clinical trials of another drug and may not reflect the rates observed in clinical practice.

The safety of LIPOFEN has been established in adults with hypertriglyceridemia or primary hyperlipidemia based on adequate and well-controlled trials of other formulations of fenofibrate, referenced below as "fenofibrate" [see Clinical Studies (14)]. Dosages of fenofibrate used in these trials were comparable to LIPOFEN 150 mg per day [see Clinical Pharmacology (12.3)].

Adverse reactions reported by 2% or more of patients treated with fenofibrate (and greater than placebo) during the double-blind, placebo-controlled trials are listed in Table 1 below. Adverse reactions led to discontinuation of treatment in 5% of patients treated with fenofibrate and in 3% treated with placebo. Increases in liver function tests were the most frequent events, causing discontinuation of fenofibrate treatment in 1.6% of patients in double-blind trials.

Table 1: Adverse Reactions Reported by 2% or More of Patients Treated with Fenofibrate and Greater than Placebo During the Double-Blind, Placebo-Controlled Trials
Adverse Reaction | Placebo (N =365) | Fenofibrate (N = 439)
Abnormal Liver Tests | 1% | 8%
Abdominal Pain | 4% | 5%
Increased ALT | 2% | 3%
Increased AST | 1% | 3%
Increased Creatine Phosphokinase | 1% | 3%
Constipation | 1% | 2%
Rhinitis | 1% | 2%

Other Adverse Reactions

Urticaria

Urticaria was seen in 1.1% vs. 0% and rash in 1.4% vs. 0.8% of fenofibrate and placebo patients respectively in controlled trials.

Increases in Liver Enzymes

In a pooled analysis of 10 placebo controlled trials, increases to > 3 times the upper limit of normal in ALT occurred in 5.3% of patients taking either an intermediate or the maximum recommended daily dosage of fenofibrate versus 1.1% of patients treated with placebo. In an 8-week trial, the incidence of ALT or AST elevations ≥ 3 times the upper limit of normal was 13% in patients receiving an intermediate daily dosage or the maximum recommended daily dosage of fenofibrate and was 0% in those receiving the lowest recommended daily dosage of fenofibrate or placebo [see Warnings and Precautions (5.2)].

6.2 Postmarketing Experience

The following adverse reactions have been identified during post-approval use of fenofibrate. Because these reactions are reported voluntarily from a population of uncertain size, it is not always possible to reliably estimate their frequency or establish a causal relationship to drug exposure:

Blood: Anemia, white blood cell decreases

Gastrointestinal: Pancreatitis

General: Asthenia

Hepatobiliary: Increased total bilirubin, hepatitis, cirrhosis

Immune System: Anaphylaxis, angioedema

Lipid Disorders: Severely depressed HDL-cholesterol levels

Musculoskeletal: Myalgia, muscle spasms, rhabdomyolysis, arthralgia

Renal and Urinary: Acute renal failure

Respiratory: Interstitial lung disease

Skin and Subcutaneous Tissue: Photosensitivity reactions, days to months after initiation. This may occur in patients who report a prior photosensitivity reaction to ketoprofen.

7 DRUG INTERACTIONS

Table 2 presents clinically important drug interactions with LIPOFEN.

Table 2: Clinically Important Drug Interactions with LIPOFEN
Statins
Clinical Impact: | Fibrates may cause myopathy when given alone. The risk of myopathy and rhabdomyolysis is increased with concomitant use of fibrates with statins.
Intervention: | Consider if the benefit of using LIPOFEN concomitantly with statin therapy outweighs the increased risk of myopathy and rhabdomyolysis. If concomitant use is decided, monitor patients for signs and symptoms of myopathy, particularly during initiation of therapy and during upward dosage titration of statin therapy.
Colchicine
Clinical Impact: | Cases of myopathy and rhabdomyolysis have been reported with concomitant use of colchicine with fenofibrates.
Intervention: | Consider if the benefit of using colchicine concomitantly with LIPOFEN outweighs the increased risk of myopathy and rhabdomyolysis. If concomitant use is decided, monitor patients for signs and symptoms of myopathy, particularly during initiation of therapy and during upward dosage titration of colchicine.
Coumarin Anticoagulants
Clinical Impact: | Fibrates may cause potentiation of coumarin-type anticoagulant effects with prolongation of the PT/INR.
Intervention: | Caution should be exercised when coumarin anticoagulants are given in conjunction with LIPOFEN. The dosage of the anticoagulants should be reduced to maintain the PT/INR at the desired level to prevent bleeding complications. Frequent PT/INR determinations are advisable until it has been definitely determined that the PT/INR has stabilized
Immunosuppressants
Clinical Impact: | Immunosuppressants such as cyclosporine and tacrolimus can produce nephrotoxicity with decreases in creatinine clearance and rises in serum creatinine, and because renal excretion is the primary elimination route of fibrate drugs including LIPOFEN, there is a risk that an interaction will lead to deterioration of renal function.
Intervention: | The benefits and risks of using LIPOFEN with immunosuppressants and other potentially nephrotoxic agents should be carefully considered, and the lowest effective dosage employed and renal function monitored.
Bile-Acid Binding Resins
Clinical Impact: | Bile-acid binding resins may bind other drugs given concurrently.
Intervention: | In patients taking a bile acid resin, administer LIPOFEN at least 1 hour before or 4 to 6 hours after the bile acid resin to avoid impeding its absorption.

8 USE IN SPECIFIC POPULATIONS

8.1 Pregnancy

Risk Summary

Limited available data with fenofibrate use in pregnant women are insufficient to determine a drug associated risk of major birth defects, miscarriage or adverse maternal or fetal outcomes. In animal reproduction studies, no evidence of embryo-fetal toxicity was observed with oral administration of fenofibrate in rats and rabbits during organogenesis at doses less than or comparable to the maximum recommended clinical dosage of 150 mg daily, based on body surface area (mg/m^2). Adverse reproductive outcomes occurred at higher doses in the presence of maternal toxicity (see Data). LIPOFEN should be used during pregnancy only if the potential benefit justifies the potential risk to the fetus.

The estimated background risk of major birth defects and miscarriage for the indicated population is unknown. In the U.S. general population, the estimated background risk of major birth defects and miscarriage in clinically recognized pregnancies is 2 to 4% and 15 to 20%, respectively.

Data

Animal Data

In pregnant rats given oral dietary doses of 14 mg/kg/day, 127 mg/kg/day, and 361 mg/kg/day from gestation day 6 to 15 during the period of organogenesis, no adverse developmental findings were observed at 14 mg/kg/day (less than the clinical exposure at the maximum recommended human dose [MRHD] of 300 mg fenofibrate daily, comparable to 150 mg LIPOFEN daily, based on body surface area comparisons). Increased fetal skeletal malformations were observed at maternally toxic doses (361 mg/kg/day, corresponding to 12 times the clinical exposure at the MRHD) that significantly suppressed maternal body weight gain.

In pregnant rabbits given oral gavage doses of 15 mg/kg/day, 150 mg/kg/day, and 300 mg/kg/day from gestation day 6 to 18 during the period of organogenesis and allowed to deliver, no adverse developmental findings were observed at 15 mg/kg/day (a dose that approximates the clinical exposure at the MRHD, based on body surface area comparisons). Aborted litters were observed at maternally toxic doses (≥ 150 mg/kg/day, corresponding to ≥ 10 times the clinical exposure at the MRHD) that suppressed maternal body weight gain.

In pregnant rats given oral dietary doses of 15 mg/kg/day, 75 mg/kg/day, and 300 mg/kg/day from gestation day 15 through lactation day 21 (weaning), no adverse developmental effects were observed at 15 mg/kg/day (less than the clinical exposure at the MRHD, based on body surface area comparisons), despite maternal toxicity (decreased weight gain). Post-implantation loss was observed at ≥ 75 mg/kg/day (≥ 2 times the clinical exposure at the MRHD) in the presence of maternal toxicity (decreased weight gain). Decreased pup survival was noted at 300 mg/kg/day (10 times the clinical exposure at the MRHD), which was associated with decreased maternal body weight gain/maternal neglect.

8.2 Lactation

Risk Summary

There is no available information on the presence of fenofibrate in human milk, effects of the drug on the breastfed infant, or the effects on milk production. Fenofibrate is present in the milk of rats, and is therefore likely to be present in human milk. Because of the potential for serious adverse reactions in breastfed infants, such as disruption of infant lipid metabolism, women should not breastfeed during treatment with LIPOFEN and for 5 days after the final dose

8.4 Pediatric Use

The safety and effectiveness of LIPOFEN have not been established in pediatric patients with severe hypertriglyceridemia or primary hyperlipidemia.

8.5 Geriatric Use

Assess renal function in geriatric patients and follow contraindications and dosing recommendations for patients with renal impairment [see Contraindications (4), Warnings and Precautions (5.3, 5.4), and Use in Specific Populations (8.6). While fenofibric acid exposure is not influenced by age, geriatric patients are more likely to have renal impairment, and fenofibric acid is substantially excreted by the kidney [see Clinical Pharmacology (12.3)].

Consider monitoring renal function in geriatric patients taking LIPOFEN.

8.6 Renal Impairment

LIPOFEN is contraindicated in patients with severe renal impairment (eGFR <30 mL/min/1.73m^2) including those with end-stage renal disease (ESRD) and those receiving dialysis. Dosage reduction is required in patients with mild to moderate renal impairment [see Dosage and Administration (2.4) and Clinical Pharmacology (12.3)]. Patients with severe renal impairment have 2.7-fold higher exposure of fenofibric acid and increased accumulation of fenofibric acid during chronic dosing compared with healthy volunteers. Renal impairment is a risk factor for myopathy and rhabdomyolysis [see Warnings and Precautions (5.3, 5.4), and Clinical Pharmacology (12.3)].

8.7 Hepatic Impairment

The use of LIPOFEN has not been evaluated in patients with hepatic impairment. LIPOFEN is contraindicated in patients with active liver disease, including those with unexplained persistent liver function abnormalities [Clinical Pharmacology (12.3)].

10 OVERDOSAGE

In the event of an overdose of LIPOFEN, consider contacting the Poison Help line (1-800-222-1222) or a medical toxicologist for additional overdosage management recommendations.

There is no specific treatment for overdose with LIPOFEN. General supportive care of the patient is indicated, including monitoring of vital signs and observation of clinical status, should an overdose occur. If indicated, elimination of unabsorbed drug should be achieved by emesis or gastric lavage, usual precautions should be observed to maintain the airway. Because fenofibric acid is highly bound to plasma proteins, hemodialysis should not be considered.

11 DESCRIPTION

LIPOFEN® (fenofibrate capsules, USP), is a peroxisome proliferator-activated receptor (PPAR) alpha agonist available as hard gelatin capsules for oral administration. Each hard gelatin capsule contains 50 or 150 mg of fenofibrate USP. The chemical name for fenofibrate is 2-[4-(4-chlorobenzoyl) phenoxy]-2-methyl-propanoic acid, 1-methylethyl ester with the following structural formula:

The empirical formula is C20H21O4Cl and the molecular weight is 360.83; fenofibrate is insoluble in water. The melting point is 79-82°C. Fenofibrate is a white solid which is stable under ordinary conditions.

LIPOFEN (fenofibrate capsules, USP) meets USP Dissolution Test 2.

Inactive Ingredients: Each hard gelatin capsule contains Gelucire 44/14 (lauroyl macrogol glyceride type 1500), polyethylene glycol 20,000, polyethylene glycol 8000, hydroxypropylcellulose, sodium starch glycolate, gelatin, titanium dioxide, shellac, propylene glycol, may also contain black iron oxide, FD&C Blue #1, FD&C Blue #2, FD&C Red #40, D&C Yellow #10.

12 CLINICAL PHARMACOLOGY

12.1 Mechanism of Action

The active moiety of LIPOFEN is fenofibric acid. The pharmacological effects of fenofibric acid in both animals and humans have been studied through oral administration of fenofibrate.

The lipid-modifying effects of fenofibric acid seen in clinical practice have been explained in vivo in transgenic mice and in vitro in human hepatocyte cultures by the activation of PPAR alpha receptor. Through this mechanism, fenofibric acid increases lipolysis and elimination of triglyceride-rich particles from plasma by activating lipoprotein lipase and reducing production of apoprotein C-III (an inhibitor of lipoprotein lipase activity).

12.2 Pharmacodynamics

Fenofibric acid, the active metabolite of fenofibrate, produces reductions in total cholesterol (Total-C), total triglycerides, and triglyceride rich lipoprotein (VLDL) in treated patients with severe hypertriglyceridemia.

12.3 Pharmacokinetics

Fenofibrate is a pro-drug of the active chemical moiety fenofibric acid. Fenofibrate is converted by ester hydrolysis in the body to fenofibric acid which is the active constituent measurable in the circulation. In a study of LIPOFEN capsules 200 mg, following single-dose administration, the plasma concentration (AUC) for the parent compound fenofibrate was approximately 40 µg/mL compared to 204 µg/mL for the metabolite, fenofibric acid. In the same study, the half-life was observed to be 0.91 hours for the parent compound versus 16.76 hours for the metabolite.

Absorption

The absolute bioavailability of fenofibrate cannot be determined as the compound is virtually insoluble in aqueous media suitable for injection. However, fenofibrate is well absorbed from the gastrointestinal tract. Peak plasma levels of fenofibric acid occur within approximately 5 hours after oral administration.

In a single dose and multiple dose study with LIPOFEN capsules 200 mg, the extent of absorption (AUC) of fenofibric acid, the principal metabolite of fenofibrate, was 42% larger at steady state compared to single-dose administration. The rate of absorption (Cmax) of fenofibric acid was 73% greater after multiple-dose than after single-dose administration.

The extent of absorption of LIPOFEN in terms of AUC value of fenofibric acid increased in a less than proportional manner while the rate of absorption in terms of Cmax value of fenofibric acid increased proportionally related to dose.

Effect of Food

The absorption of fenofibrate is increased when administered with food. With LIPOFEN, the extent of absorption is increased by approximately 58% and 25% under high-fat fed and low-fat fed conditions as compared to fasting conditions, respectively.

Distribution

Upon multiple dosing of fenofibrate, fenofibric acid steady state is achieved after 5 days. Plasma concentrations of fenofibric acid at steady state are approximately double of those following a single dose. Serum protein binding was approximately 99% in normal and hyperlipidemic subjects.

Elimination

Fenofibric acid is eliminated with a half-life of approximately 20 hours allowing once daily dosing of LIPOFEN.

Metabolism

Following oral administration, fenofibrate is rapidly hydrolyzed by esterases to the active metabolite, fenofibric acid; unchanged fenofibrate is detected at low concentrations in plasma compared to fenofibric acid over most of the single dose and multiple dosing periods.

Fenofibric acid is primarily conjugated with glucuronic acid and then excreted in urine. A small amount of fenofibric acid is reduced at the carbonyl moiety to a benzhydrol metabolite which is, in turn, conjugated with glucuronic acid and excreted in urine.

In vitro and in vivo metabolism data indicate that neither fenofibrate nor fenofibric acid undergo oxidative metabolism (e.g., cytochrome P450) to a significant extent.

Excretion

After absorption, fenofibrate is mainly excreted in the urine in the form of metabolites, primarily fenofibric acid and fenofibric acid glucuronide. After oral administration of a single dose of radiolabeled fenofibrate in healthy volunteers, approximately 60% of the dose appeared in the urine, primarily as fenofibric acid and its glucuronide conjugate, and 25% was excreted in feces.

Use in Specific Populations

Geriatric Patients

In geriatric volunteers 77 to 87 years of age, the apparent oral clearance of fenofibric acid following a single oral dose of fenofibrate was 1.2 L/h, which compares to 1.1 L/h in young adults. This indicates that an similar dosage regimen can be used in geriatric patients with normal renal function, without increasing accumulation of the drug or metabolites [see Dosage and Administration (2) and Use in Specific Populations (8)].

Pediatric Patients

Pharmacokinetics of LIPOFEN has not been studied in pediatric patients.

Male and Female Patients

No pharmacokinetic difference between males and females has been observed for fenofibrate.

Racial or Ethnic Groups

The influence of race on the pharmacokinetics of fenofibrate has not been studied, however fenofibrate is not metabolized by enzymes known for exhibiting inter-ethnic variability.

Patients with Renal Impairment

The pharmacokinetics of fenofibric acid were examined in patients with mild, moderate and severe renal impairment. Patients with severe renal impairment (creatinine clearance [CrCl ≤30 mL/min] <30 mL/min or estimated glomerular filtration rate [eGFR] <30 mL/min/1.73m^2) showed a 2.7-fold increase in exposure for fenofibric acid and increased accumulation of fenofibric acid during chronic dosing compared to that of healthy subjects. Patients with mild to moderate renal impairment (CrCl 30 mL/min to 80 mL/min or eGFR 30 to 59 mL/min/1.73m^2) had similar exposure but an increase in the half-life for fenofibric acid compared to that of healthy subjects.

Patients with Hepatic Impairment

No pharmacokinetic studies have been conducted in patients with hepatic impairment.

Drug Interaction Studies

In vitro studies using human liver microsomes indicate that fenofibrate and fenofibric acid are not inhibitors of cytochrome (CYP) P450 isoforms CYP3A4, CYP2D6, CYP2E1, or CYP1A2. They are weak inhibitors of CYP2C8, CYP2C19 and CYP2A6, and mild to moderate inhibitors of CYP2C9 at therapeutic concentrations.

Table 3 describes the effects of co-administered drugs on fenofibric acid systemic exposure.

Table 4 describes the effects of co-administered fenofibrate or fenofibric acid on systemic exposure of other drugs.

Table 3: Effects of Co-Administered Drugs on Fenofibric Acid Systemic Exposure from Fenofibrate Administration
Co-Administered Drug | Dosage Regimen of Co-Administered Drug | Dosage Regimen of Fenofibrate | Changes in Fenofibric Acid Exposure
Co-Administered Drug | Dosage Regimen of Co-Administered Drug | Dosage Regimen of Fenofibrate | AUC | Cmax
Lipid-lowering medications
Atorvastatin | 20 mg once daily for 10 days | Fenofibrate 160 mg [TriCor (fenofibrate) oral tablet] once daily for 10 days | ↓2% | ↓4%
Pravastatin | 40 mg as a single dose | Fenofibrate 3 × 67 mg [TriCor (fenofibrate) oral micronized capsule] as a single dose | ↓1% | ↓2%
Fluvastatin | 40 mg as a single dose | Fenofibrate 160 mg as a single dose | ↓2% | ↓10%
Anti-diabetic medications
Glimepiride | 1 mg as a single dose | Fenofibrate 145 mg once daily for 10 days | ↑1% | ↓1%
Metformin | 850 mg three times daily for 10 days | Fenofibrate 54 mg three times daily for 10 days | ↓9% | ↓6%
Rosiglitazone | 8 mg once daily for 5 days | Fenofibrate 145 mg once daily for 14 days | ↑10% | ↑3%

Table 4: Effects of Fenofibrate on Systemic Exposure of Other Drugs
Dosage Regimen of Fenofibrate | Dosage Regimen of Co-Administered Drug | Changes in Co-Administered Drug Exposure
Dosage Regimen of Fenofibrate | Dosage Regimen of Co-Administered Drug | Analyte | AUC | Cmax
Lipid-lowering medications
Fenofibrate 160 mg [TriCor (fenofibrate) oral tablet] once daily for 10 days | Atorvastatin, 20 mg once daily for 10 days | Atorvastatin | ↓17% | 0%
Fenofibrate 3 × 67 mg [TriCor (fenofibrate) oral micronized capsule] as a single dose | Pravastatin, 40 mg as a single dose | Pravastatin | ↑13% | ↑13%
 |  | 3α-Hydroxyl-iso-pravastatin | ↑26% | ↑29%
Fenofibrate 160 mg as a single dose | Fluvastatin, 40 mg as a single dose | (+)-3R, 5S-Fluvastatin | ↑15% | ↑16%
Anti-diabetic medications
Fenofibrate 145 mg once daily for 10 days | Glimepiride, 1 mg as a single dose | Glimepiride | ↑35% | ↑18%
Fenofibrate 54 mg three times daily for 10 days | Metformin, 850 mg three times daily for 10 days | Metformin | ↑3% | ↑6%
Fenofibrate 145 mg once daily for 14 days | Rosiglitazone, 8 mg once daily for 5 days | Rosiglitazone | ↑6% | ↓1%

13 NONCLINICAL TOXICOLOGY

13.1 Carcinogenesis, Mutagenesis, and Impairment of Fertility

Carcinogenesis: Two dietary carcinogenicity studies have been conducted in rats with fenofibrate. In the first 24-month study, Wistar rats were dosed with fenofibrate at 10 mg/kg/day, 45 mg/kg/day, and 200 mg/kg/day, approximately 0.3 times, 1 time, and 6 times the maximum recommended human dose (MRHD) based on body surface area comparisons (mg/m^2). At a dose of 200 mg/kg/day (at 6 times the MRHD), the incidence of liver carcinomas was significantly increased in both sexes. A statistically significant increase in pancreatic carcinomas was observed in males at 1 and 6 times the MRHD; an increase in pancreatic adenomas and benign testicular interstitial cell tumors was observed at 6 times the MRHD in males. In a second 24-month study in a different strain of rats (Sprague-Dawley), doses of 10 mg/kg/day and 60 mg/kg/day (0.3 and 2 times the MRHD) produced significant increases in the incidence of pancreatic acinar adenomas in both sexes and increases in testicular interstitial cell tumors in males at 2 times the MRHD.

A 117-week carcinogenicity study was conducted in rats comparing three drugs: fenofibrate 10 mg/kg/day and 60 mg/kg/day (0.3 and 2 times the MRHD), clofibrate (400 mg/kg/day; 2 times the human dose), and gemfibrozil (250 mg/kg/day; 2 times the human dose, based on mg/m^2 surface area). Fenofibrate increased pancreatic acinar adenomas in both sexes. Clofibrate increased hepatocellular carcinoma and pancreatic acinar adenomas in males and hepatic neoplastic nodules in females. Gemfibrozil increased hepatic neoplastic nodules in males and females, while all three drugs increased testicular interstitial cell tumors in males.

In a 21-month study in CF-1 mice, fenofibrate 10 mg/kg/day, 45 mg/kg/day, and 200 mg/kg/day (approximately 0.2 times, 1 time, and 3 times the MRHD on the basis of mg/m^2 surface area) significantly increased the liver carcinomas in both sexes at 3 times the MRHD. In a second 18-month study at 10 mg/kg/day, 60 mg/kg/day, and 200 mg/kg/day, fenofibrate significantly increased the liver carcinomas in male mice and liver adenomas in female mice at 3 times the MRHD.

Electron microscopy studies have demonstrated peroxisomal proliferation following fenofibrate administration to the rat. An adequate study to test for peroxisome proliferation in humans has not been done, but changes in peroxisome morphology and numbers have been observed in humans after treatment with other members of the fibrate class when liver biopsies were compared before and after treatment in the same individual.

Mutagenesis: Fenofibrate has been demonstrated to be devoid of mutagenic potential in the following tests: Ames, mouse lymphoma, chromosomal aberration and unscheduled DNA synthesis in primary rat hepatocytes.

Impairment of Fertility: In fertility studies rats were given oral dietary doses of fenofibrate, males received 61 days prior to mating and females 15 days prior to mating through weaning which resulted in no adverse effect on fertility at doses up to 300 mg/kg/day (approximately 10 times the MRHD, based on body surface area comparisons).

14 CLINICAL STUDIES

14.1 Overview of Clinical Trials

The effectiveness of LIPOFEN has been established in adults with hypertriglyceridemia or primary hyperlipidemia based on adequate and well-controlled trials of other formulations of fenofibrate, referenced below as "fenofibrate." Dosages of fenofibrate used in these trials were comparable to LIPOFEN 150 mg per day [see Clinical Pharmacology (12.3)].

14.2 Clinical Trials in Adults with Hypertriglyceridemia

The effects of fenofibrate on serum TG were studied in two randomized, double-blind, placebo-controlled clinical trials of 147 patients with hypertriglyceridemia. Patients were treated for 8 weeks under protocols that differed only in that one entered patients with baseline TG levels of 500 to 1,500 mg/dL, and the other TG levels of 350 to 499 mg/dL. In patients with hypertriglyceridemia and normal cholesterolemia with or without hyperchylomicronemia, treatment with fenofibrate decreased primarily very low density lipoprotein (VLDL), TG, and VLDL cholesterol (VLDL-C). Treatment of patients with elevated TG often results in an increase of LDL-C (see Table 5).

Table 5: Effects of Fenofibrate in Patients with Hypertriglyceridemia
Trial 1 | Placebo |  |  |  | Fenofibrate
Baseline TG Levels 350 to 499 mg/dL | N | Baseline Mean (mg/dL) | Endpoint Mean (mg/dL) | Mean % Change | N | Baseline Mean (mg/dL) | Endpoint Mean (mg/dL) | Mean % Change
TG | 28 | 449 | 450 | -0.5 | 27 | 432 | 223 | -46.2 [p<0.05 vs. Placebo]
VLDL-TG | 19 | 367 | 350 | 2.7 | 19 | 350 | 178 | -44.1
Total-C | 28 | 255 | 261 | 2.8 | 27 | 252 | 227 | -9.1
HDL-C | 28 | 35 | 36 | 4 | 27 | 34 | 40 | 19.6
LDL-C | 28 | 120 | 129 | 12 | 27 | 128 | 137 | 14.5
VLDL-C | 27 | 99 | 99 | 5.8 | 27 | 92 | 46 | -44.7
Trial 2 | Placebo |  |  |  | Fenofibrate
Baseline TG Levels 500 to 1500 mg/dL | N | Baseline Mean (mg/dL) | Endpoint Mean (mg/dL) | Mean % Change | N | Baseline Mean (mg/dL) | Endpoint Mean (mg/dL) | Mean % Change
TG | 44 | 710 | 750 | 7.2 | 48 | 726 | 308 | -54.5
VLDL-TG | 29 | 537 | 571 | 18.7 | 33 | 543 | 205 | -50.6
Total-C | 44 | 272 | 271 | 0.4 | 48 | 261 | 223 | -13.8
HDL-C | 44 | 27 | 28 | 5.0 | 48 | 30 | 36 | 22.9
LDL-C | 42 | 100 | 90 | -4.2 | 45 | 103 | 131 | 45.0
VLDL-C | 42 | 137 | 142 | 11.0 | 45 | 126 | 54 | -49.4

14.3 Clinical Trials in Adults with Primary Hyperlipidemia

The effects of fenofibrate were assessed in four randomized, placebo-controlled, double-blind, parallel-group trials in patients with hyperlipidemia and mixed dyslipidemia. Fenofibrate therapy reduced LDL-C, Total-C, and TG, and increased HDL-C (see Table 6).

Table 6: Mean Percent Change in Lipid Parameters at End of Treatment [Duration of study treatment was 3 to 6 months.]
Treatment Group | Total-C | LDL-C | HDL-C | TG
Mean baseline lipid values (n=646) | 306.9 mg/dL | 213.8 mg/dL | 52.3 mg/dL | 191.0 mg/dL
All fenofibrate (n=361) | -18.7% [p = <0.05 vs. Placebo] | -20.6% | +11.0% | -28.9%
Placebo (n=285) | -0.4% | -2.2% | +0.7% | +7.7%

14.4 Lack of Efficacy in Cardiovascular Outcomes Trials

Fenofibrate did not reduce cardiovascular disease morbidity or mortality in two large, randomized controlled trials of patients with type 2 diabetes mellitus.

The Action to Control Cardiovascular Risk in Diabetes Lipid (ACCORD Lipid) (NCT00000620) trial was a randomized placebo-controlled trial of 5,518 patients (2,765 assigned to receive fenofibrate) with type 2 diabetes mellitus on background statin therapy treated with fenofibrate. The mean age at baseline was 62 years and 31% were female. Overall, 68% were White, 15% were Black or African American; 7% identified as Hispanic or Latino ethnicity. The mean duration of follow-up was 4.7 years. The primary outcome of major adverse cardiovascular events (MACE), a composite of non-fatal myocardial infarction, non-fatal stroke, and cardiovascular disease death was a HR of 0.92 (95% CI, 0.79 to 1.08) for fenofibrate plus statin combination therapy as compared to statin monotherapy.

The Fenofibrate Intervention and Event Lowering in Diabetes (FIELD) trial was a 5-year randomized, placebo-controlled trial of 9,795 patients (4,895 assigned to receive fenofibrate) with type 2 diabetes mellitus treated with fenofibrate. The mean age at baseline was 62 years, 37% were female, and 93% were White. The primary outcome of coronary heart disease events was a HR of 0.89 (95% CI, 0.75 to 1.05) with fenofibrate compared to placebo. The HR for total and coronary heart disease mortality, respectively, was 1.11 (95% CI, 0.95 to 1.29) and 1.19 (95% CI, 0.90 to 1.57) with fenofibrate as compared to placebo.

Because of chemical, pharmacological, and clinical similarities between fenofibrate and pemafibrate, findings in a large randomized, placebo-controlled clinical trial with pemafibrate are relevant for LIPOFEN.

Pemafibrate did not reduce cardiovascular disease morbidity or mortality in a large, randomized, placebo-controlled trial of patients with type 2 diabetes mellitus (TG levels of 200 to 499 mg per deciliter and HDL-C levels of 40 mg per deciliter or lower), on background statin therapy (NCT03071692). The trial was a randomized placebo-controlled trial of 10,497 patients (5,240 assigned to receive pemafibrate) with type 2 diabetes mellitus on background lipid-lowering therapy. The median age at baseline was 64 years and 28% were female. Overall, 86% were White, 5% were Asian, 3% were Black or African American; 19% identified as Hispanic or Latino ethnicity. The median duration of follow-up was 3.4 years. The primary outcome of major adverse cardiovascular events (MACE), a composite of non-fatal myocardial infarction, non-fatal ischemic stroke, coronary revascularization, and death from cardiovascular causes, was a HR of 1.03 (95% CI, 0.91 to 1.15) for pemafibrate plus statin combination therapy as compared to statin monotherapy.

16 HOW SUPPLIED/STORAGE AND HANDLING

LIPOFEN® (fenofibrate) capsules is available in two strengths:

Strength | Description | NDC | Package Size (capsules per bottle)
50 mg | Size 3 white opaque/white opaque gelatin capsule, imprinted in black ink with "50" between lines on the body, "G 246" on the cap and containing a white to almost white paste | NDC 62559-305-90 | 90
150 mg | Size 1 white opaque/white opaque gelatin capsule, imprinted in green ink with "150" between lines on the body, "G 248" on the cap and containing a white to almost white paste | NDC 62559-306-90 | 90

Storage

Store at 25ºC; Excursions permitted to 15ºC - 30ºC (59ºF - 86ºF). [See USP Controlled Room Temperature]. Keep out of the reach of children. Protect from moisture and light.

17 PATIENT COUNSELING INFORMATION

Hepatotoxicity

Inform patients that LIPOFEN may cause liver enzyme elevations and possibly liver failure. Advise patients to promptly report fatigue, anorexia, right upper abdominal discomfort, dark urine or jaundice [see Contraindications (4) and Warnings and Precautions (5.2)].

Myopathy and Rhabdomyolysis

Advise patients that LIPOFEN may cause myopathy and rhabdomyolysis. Inform patients that the risk is also increased when taking certain types of medication and they should discuss all medication, both prescription and over the counter, with their healthcare provider. Instruct patients to inform other healthcare providers prescribing a new medication or increasing the dosage of an existing medication that they are taking LIPOFEN. Instruct patients to promptly report any unexplained muscle pain, tenderness, or weakness particularly if accompanied by malaise or fever [see Warnings and Precautions (5.3) and Drug Interactions (7)].

Increased Bleeding Risk with Coumarin Anticoagulants

Inform patients that the concomitant use of LIPOFEN with coumarin-type anticoagulants may increase the risk of bleeding. Advise patients if they are taking or planning to take coumarin-type anticoagulants to inform their healthcare providers and that increased monitoring may be necessary [see Warnings and Precautions (5.6) and Drug Interactions (7)].

Hypersensitivity Reactions

Inform patients that serious hypersensitivity reactions, such as anaphylaxis and angioedema, have been reported with fenofibrates. Advise patients to report immediately any signs or symptoms suggesting allergic reaction, and to discontinue drug until they have consulted prescribing physicians [see Warnings and Precautions (5.9)].

Pregnancy

Advise patients to inform their healthcare provider of a known or suspected pregnancy to discuss if LIPOFEN should be discontinued [see Use in Specific Populations (8.1)].

Lactation

Advise patients that breastfeeding during treatment with LIPOFEN is not recommended [see Use in Specific Populations (8.2)].

Missed Doses

If a dose is missed, advise patients not take an extra dose and to resume treatment with the next dose.

Product of Israel

Distributed by:
ANI Pharmaceuticals, Inc.
Baudette, MN 56623

PRINCIPAL DISPLAY PANEL - 50 mg Capsule Bottle Label

NDC 62559-305-90

Lipofen®
(fenofibrate capsules, USP)

50 mg

Rx Only

ani
Pharmaceuticals, Inc.

90 Capsules

PRINCIPAL DISPLAY PANEL - 150 mg Capsule Bottle Label

NDC 62559-306-90

Lipofen®
(fenofibrate capsules, USP)

150 mg

Rx Only

ani
Pharmaceuticals, Inc.

90 Capsules